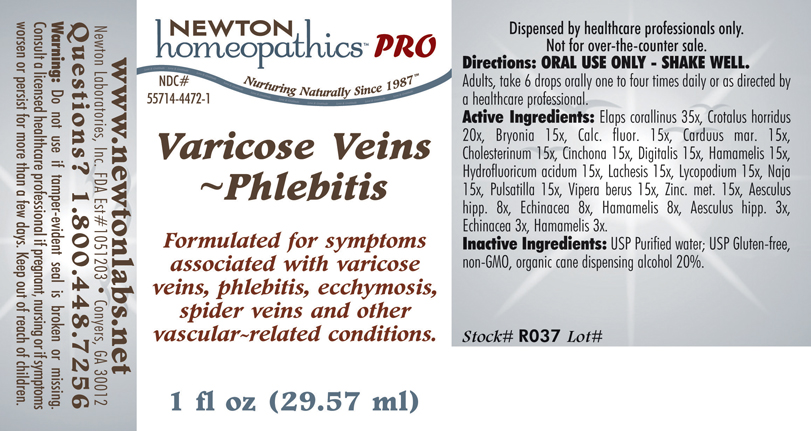 DRUG LABEL: Varicose Veins - Phlebitis 
NDC: 55714-4472 | Form: LIQUID
Manufacturer: Newton Laboratories, Inc.
Category: homeopathic | Type: HUMAN PRESCRIPTION DRUG LABEL
Date: 20110601

ACTIVE INGREDIENTS: Micrurus Corallinus Venom 35 [hp_X]/1 mL; Crotalus Horridus Horridus Venom 20 [hp_X]/1 mL; Bryonia Alba Root 15 [hp_X]/1 mL; Calcium Fluoride 15 [hp_X]/1 mL; Silybum Marianum Seed 15 [hp_X]/1 mL; Cholesterol 15 [hp_X]/1 mL; Cinchona Officinalis Bark 15 [hp_X]/1 mL; Digitalis 15 [hp_X]/1 mL; Hamamelis Virginiana Root Bark/stem Bark 15 [hp_X]/1 mL; Hydrofluoric Acid 15 [hp_X]/1 mL; Lachesis Muta Venom 15 [hp_X]/1 mL; Lycopodium Clavatum Spore 15 [hp_X]/1 mL; Naja Naja Venom 15 [hp_X]/1 mL; Pulsatilla Vulgaris 15 [hp_X]/1 mL; Vipera Berus Venom 15 [hp_X]/1 mL; Zinc 15 [hp_X]/1 mL; Horse Chestnut 8 [hp_X]/1 mL; Echinacea, Unspecified 8 [hp_X]/1 mL
INACTIVE INGREDIENTS: Alcohol

Varicose Veins - Phlebitis

PRODUCT NAME & INDICATIONS SECTION

Varicose Veins - Phlebitis Formulated for symptoms associated with varicose veins, phlebitis, ecchymosis, spider veins and other vascular - related conditions.

DIRECTION SECTION

Directions: ORAL USE ONLY - SHAKE WELL. Adults, take 6 drops orally one to four times daily or as directed by a healthcare professional.

ACTIVE INGREDIENT SECTION

Elaps corallinus 35x, Crotalus horridus 20x, Bryonia 15x, Calc. fluor. 15x, Carduus mar. 15x, Cholesterinum 15x, Cinchona 15x, Digitalis 15x, Hamamelis 15x ,Hydrofluoricum acidum 15x, Lachesis 15x, Lycopodium 15x, Naja 15x, Pulsatilla 15x, Vipera berus 15x, Zinc. met. 15x, Aesculus hipp. 8x, Echinacea 8x, Hamamelis 8x, Aesculus hipp. 3x, Echinacea 3x, Hamamelis 3x.

PURPOSE SECTION

Formulated for symptoms associated with varicose veins, phlebitis, ecchymosis, spider veins and other vascular - related conditions.

INACTIVE INGREDIENT SECTION

Inactive Ingredients: USP Purified Water; USP Gluten-free, non-GMO, organic cane dispensing alcohol 20%.

QUESTIONS? SECTION

www.newtonlabs.net Newton Laboratories, Inc. FDA Est # 1051203 - Conyers, GA 30012
Questions? 1.800.448.7256

WARNINGS SECTION

Warning: Do not use if tamper - evident seal is broken or missing. Consult a licensed healthcare professional if pregnant, nursing or if symptoms worsen or persist for more than a few days. Keep out of reach of children.

OTC - PREGNANCY OR BREAST FEEDING SECTION

Consult a licensed healthcare professional if pregnant, nursing or if symptoms worsen or persist for more than a few days.

OTC - KEEP OUT OF REACH OF CHILDREN SECTION

Keep out of reach of children.